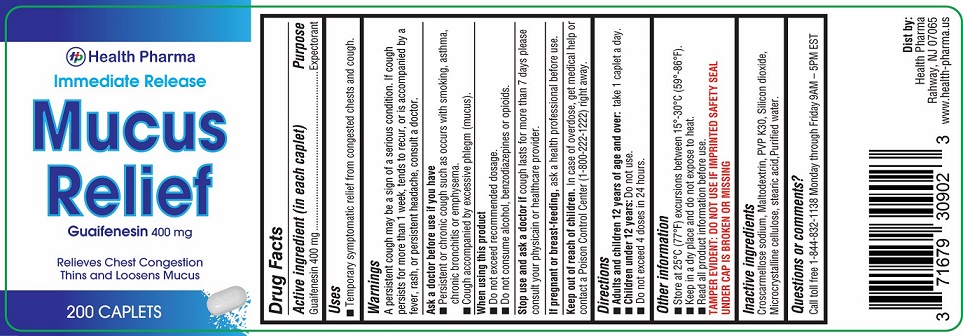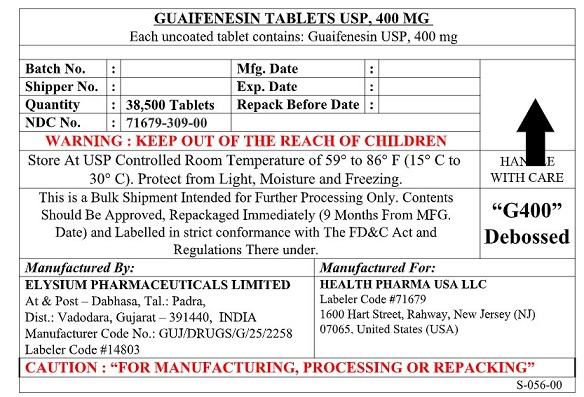 DRUG LABEL: Guaifenesin
NDC: 71679-309 | Form: TABLET
Manufacturer: Health Pharma USA LLC
Category: otc | Type: HUMAN OTC DRUG LABEL
Date: 20251205

ACTIVE INGREDIENTS: GUAIFENESIN 400 mg/1 1
INACTIVE INGREDIENTS: MALTODEXTRIN; CROSCARMELLOSE SODIUM; WATER; SILICON DIOXIDE; CELLULOSE, MICROCRYSTALLINE; STEARIC ACID; POVIDONE K30

Guaifenesin Tablets, USP 400 mg

Active ingredient (in each caplet)

Guaifenesin 400 mg

Purpose

Expectorant

Uses

- Temporary symptomatic relief from congested chests and cough.

Warnings

A persistent cough may be a sign of a serious condition. If cough persists for more than 1 week, tends to recur, or is accompanied by a fever, rash, or persistent headache, consult a doctor.

ask a doctor before use if you have

- Persistent or chronic cough such as occurs with smoking, asthma, chronic bronchitis or emphysema.
- Cough accompanied by excessive phlegm (mucus).

When using this product

- Do not exceed recommended dosage.
- Do not consume alcohol, benzodiazepines or opioids.

Stop use and ask a doctor if

cough lasts for more than 7 days please consult your physician or healthcare provider.

PREGNANCY OR BREAST FEEDING

If pregnant or breast-feeding,ask a health professional before use.

Keep out of reach of children.

In case of overdose, get medical help or contact a Poison Control Center (1-800-222-1222) right away.

Directions

- Adults and children 12 years of age and over:take 1 caplet a day.
- Children under 12 years:Do not use.
- Do not exceed 4 doses in 24 hours.

Other information
■ Store at 25°C (77°F) excursions between 15°-30°C (59°-86°F).
■ Keep in a dry place and do not expose to heat.
■ Read all product information before use.
TAMPER EVIDENT: DO NOT USE IF IMPRINTED SAFETY SEAL UNDER CAP IS BROKEN OR MISSING

Inactive ingredients
Croscarmellose sodium, Maltodextrin, PVP K30, Silicon dioxide, Microcrystalline cellulose, stearic acid, Purified water.

Questions or comments?

Call toll free 1-844-832-1138 Monday through Friday 9AM – 5PM EST